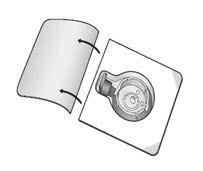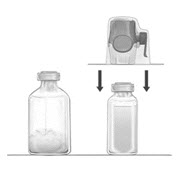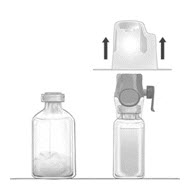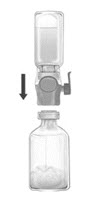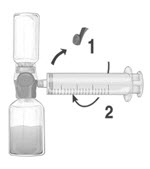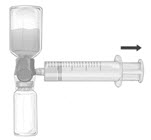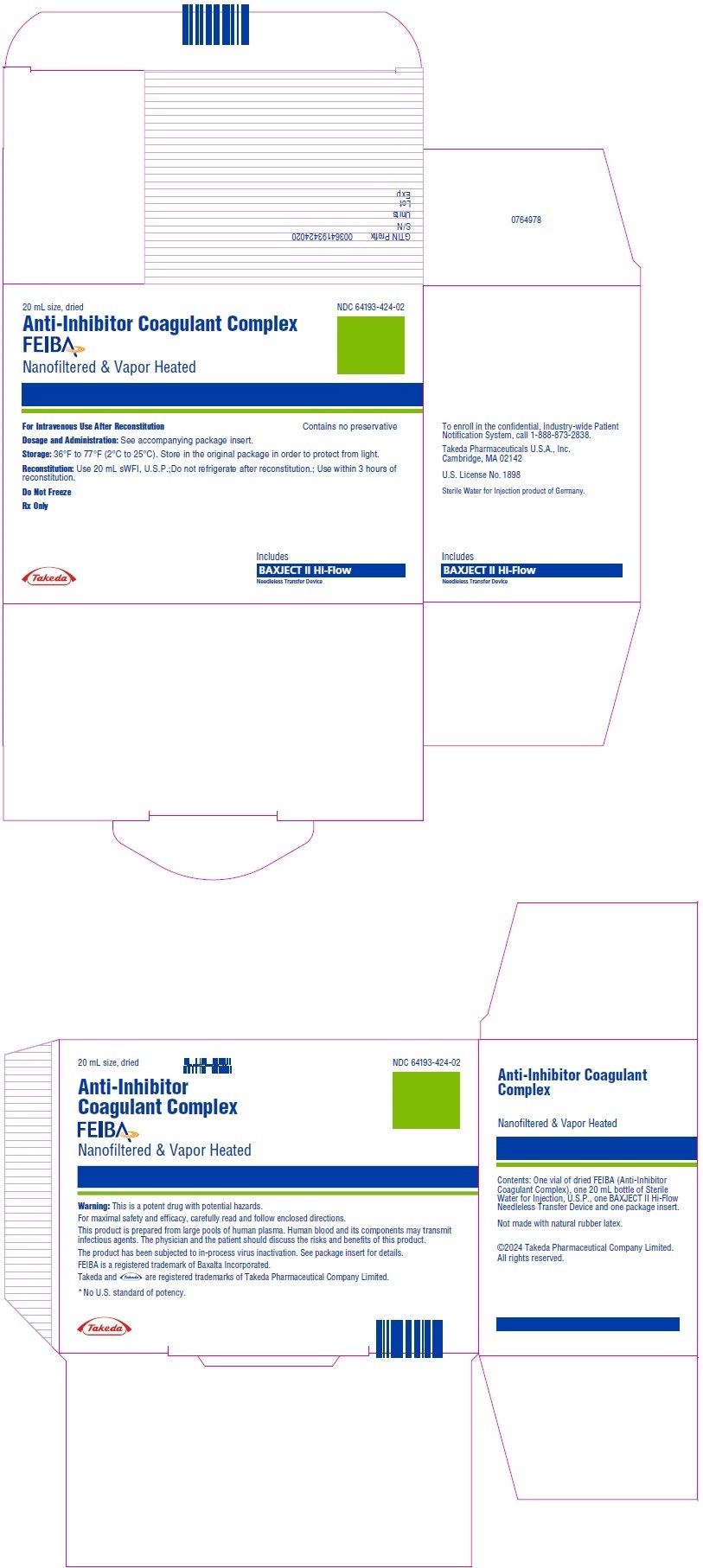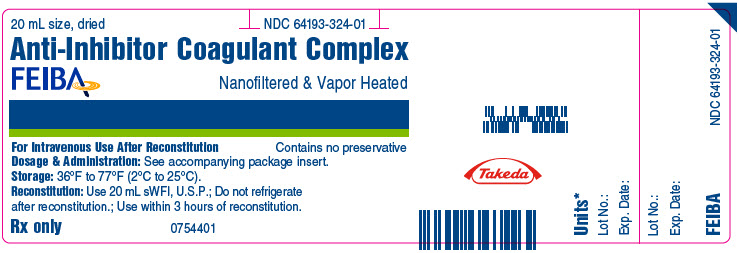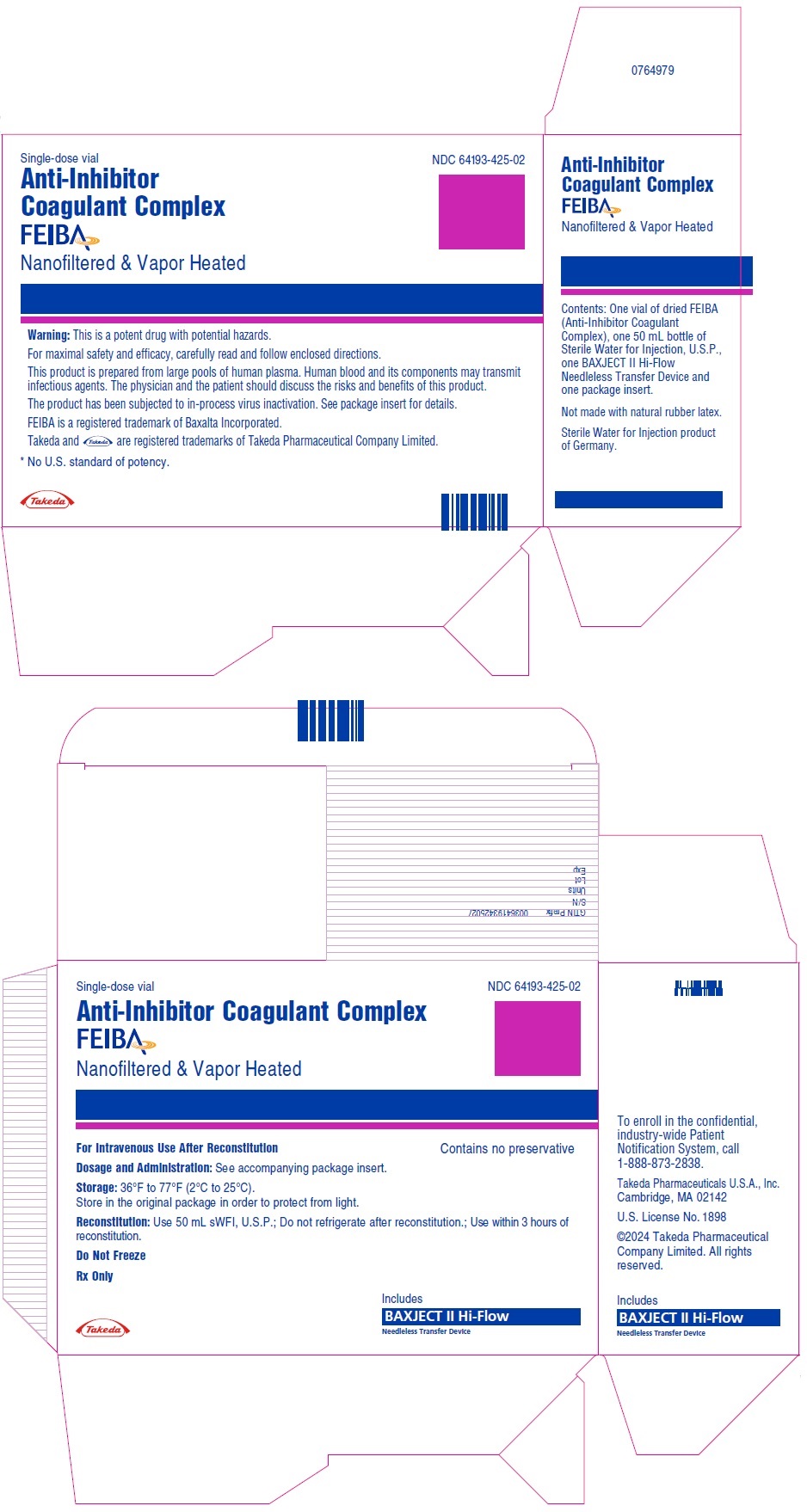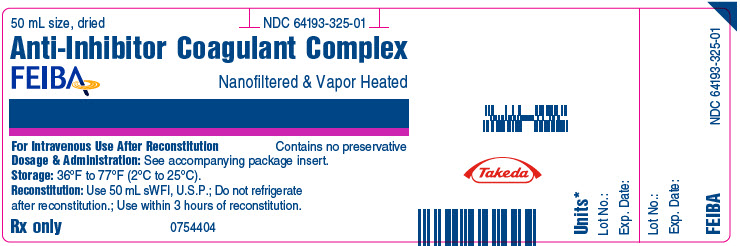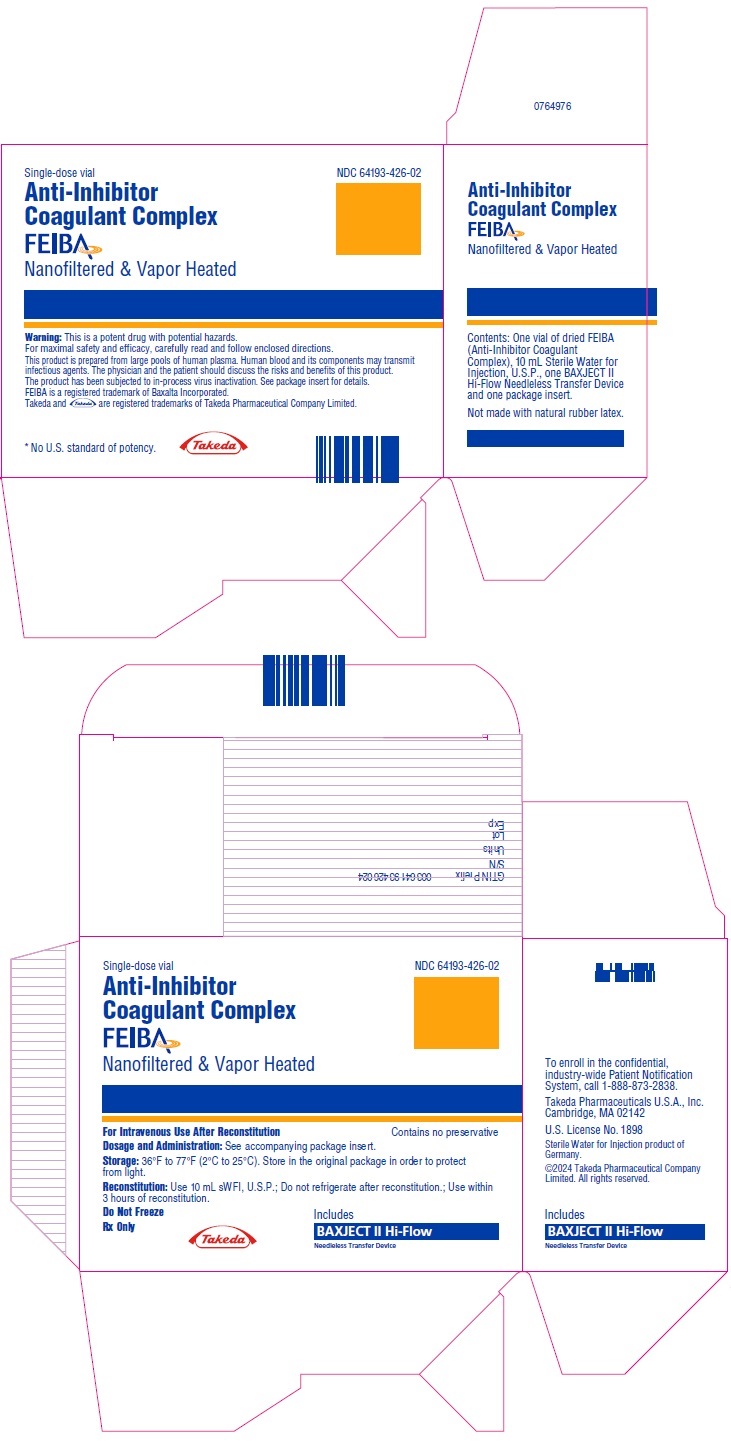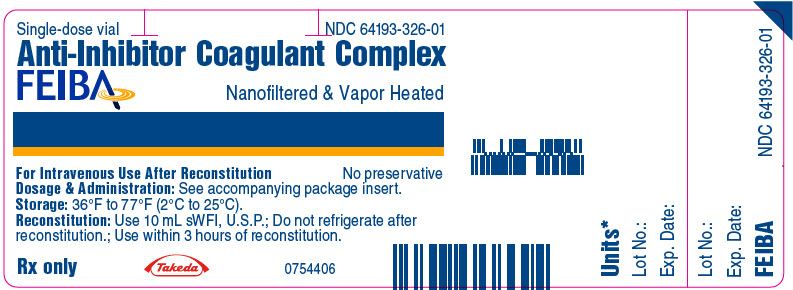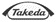 DRUG LABEL: FEIBA
NDC: 64193-424 | Form: KIT | Route: INTRAVENOUS
Manufacturer: Takeda Pharmaceuticals America, Inc.
Category: prescription | Type: HUMAN PRESCRIPTION DRUG LABEL
Date: 20251127

ACTIVE INGREDIENTS: ANTI-INHIBITOR COAGULANT COMPLEX 1000 U/20 mL
INACTIVE INGREDIENTS: TRISODIUM CITRATE DIHYDRATE; SODIUM CHLORIDE; WATER 20 mL/20 mL

HIGHLIGHTS OF PRESCRIBING INFORMATION

These highlights do not include all the information needed to use FEIBA safely and effectively. See full prescribing information for FEIBA.
FEIBA® (anti-inhibitor coagulant complex)
lyophilized powder for solution, for intravenous use
Initial U.S. Approval: 1986

RECENT MAJOR CHANGES

Dosage and Administration (2.2, 2.3) | 03/2024

WARNING: EMBOLIC and THROMBOTIC EVENTS

See full prescribing information for complete boxed warning.

- Thromboembolic events have been reported during postmarketing surveillance, particularly following the administration of high doses and/or in patients with thrombotic risk factors.
- Monitor patients receiving FEIBA for signs and symptoms of thromboembolic events (5.1, 6.2).

1 INDICATIONS AND USAGE

FEIBA is an Anti-Inhibitor Coagulant Complex indicated for use in hemophilia A and B patients with inhibitors for:

- Control and prevention of bleeding episodes.
- Perioperative management.
- Routine prophylaxis to prevent or reduce the frequency of bleeding episodes.

FEIBA is not indicated for the treatment of bleeding episodes resulting from coagulation factor deficiencies in the absence of inhibitors to factor VIII or factor IX. (1)

2 DOSAGE AND ADMINISTRATION

For intravenous use after reconstitution only (2)

- Each vial of FEIBA contains the labeled amount of factor VIII inhibitor bypassing activity in units. (2.1)

Type of Bleeding | Dose (unit/kg) | Frequency/Duration
Control and Prevention of Bleeding | 50 - 100 | Determined by the type of bleeding episode
Perioperative Management | 50 - 100 | Determined by the type of surgical intervention
Routine Prophylaxis | 85 | Every other day

Maximum injection or infusion rate must not exceed 10 units per kg of body weight per minute. (2.3)

3 DOSAGE FORMS AND STRENGTHS

FEIBA is available as a lyophilized powder in single-dose vials containing nominally 500, 1000, or 2500 units per vial. (3)

4 CONTRAINDICATIONS

- History of anaphylactic or severe hypersensitivity reactions to FEIBA or any of its components, including factors of the kinin generating system. (4)
- Disseminated intravascular coagulation (DIC). (4)
- Acute thrombosis or embolism (including myocardial infarction). (4)

5 WARNINGS AND PRECAUTIONS

- FEIBA can cause thromboembolic events following doses above 200 units per kg per day and in patients with thrombotic risk factors. Monitor patients receiving FEIBA for signs and symptoms of thromboembolic events. (5.1)
- Anaphylaxis and severe hypersensitivity reactions may occur. Should symptoms occur, discontinue treatment with FEIBA and administer appropriate treatment. (5.2)
- FEIBA is made from human plasma and may contain infectious agents, e.g., viruses, the variant Creutzfeldt-Jacob disease (vCJD) and theoretically, Creutzfeldt-Jacob disease (CJD) agent. (5.3)

6 ADVERSE REACTIONS

- The most common adverse reactions observed in >5% of subjects were anemia, diarrhea, hemarthrosis, hepatitis B surface antibody positive, nausea, and vomiting. (6.1)
- The serious adverse drug reactions are hypersensitivity and thromboembolic events, including stroke, pulmonary embolism, and deep vein thrombosis. (5.1, 5.2, 6)

To report SUSPECTED ADVERSE REACTIONS, contact Takeda Pharmaceuticals U.S.A., Inc. at 1-877-TAKEDA-7 (1-877-825-3327) or FDA at 1-800-FDA-1088 or www.fda.gov/medwatch.

7 DRUG INTERACTIONS

Consider the possibility of thrombotic events when systemic antifibrinolytics such as tranexamic acid and aminocaproic acid are used. Use of antifibrinolytics within approximately 6 to 12 hours after the administration of FEIBA is not recommended. (7)

FULL PRESCRIBING INFORMATION

WARNING: EMBOLIC and THROMBOTIC EVENTS

- Thromboembolic events have been reported during postmarketing surveillance following infusion of FEIBA, particularly following the administration of high doses and/or in patients with thrombotic risk factors.
- Monitor patients receiving FEIBA for signs and symptoms of thromboembolic events.

1 INDICATIONS AND USAGE

FEIBA is an Anti-Inhibitor Coagulant Complex indicated for use in hemophilia A and B patients with inhibitors for:

- Control and prevention of bleeding episodes
- Perioperative management
- Routine prophylaxis to prevent or reduce the frequency of bleeding episodes.

FEIBA is not indicated for the treatment of bleeding episodes resulting from coagulation factor deficiencies in the absence of inhibitors to coagulation factor VIII or coagulation factor IX.

2 DOSAGE AND ADMINISTRATION

For intravenous use after reconstitution only.

2.1 Dose

A guide for dosing FEIBA is provided in Table 1.

Table 1: Dosing Guidelines
 | Dose (unit/kg) | Frequency of Doses (hours) | Duration of Therapy
Control and Prevention of Bleeding
Joint Hemorrhage | 50 – 100 | 12 | Until pain and acute disabilities are improved.
Mucous Membrane Bleeding | 50 – 100 | 6 | At least 1 day or until bleeding is resolved.
Soft Tissue Hemorrhage (e.g., retroperitoneal bleeding) | 100 | 12 | Until resolution of bleed.
Other Severe Hemorrhage (e.g., CNS bleeds) | 100 | 6 – 12 | Until resolution of bleed.
Perioperative Management
Preoperative | 50 – 100 | One time dose | Immediately prior to surgery.
Postoperative | 50 – 100 | 6 – 12 | Until resolution of bleed and healing are achieved.
Routine Prophylaxis
 | 85 | Every other day

- Dosage and duration of treatment depend on the location and extent of bleeding, and the patient's clinical condition. Careful monitoring of replacement therapy is necessary in cases of major surgery or life-threatening bleeding episodes.
- Each vial of FEIBA contains the labeled amount of factor VIII inhibitor bypassing activity in units.
- Base the dose and frequency of FEIBA on the individual clinical response. Clinical response to treatment with FEIBA may vary by patient and may not correlate with the patient's inhibitor titer.
- Record the name of the patient and batch number of the product in order to maintain a link between the patient and the batch of the product.
- Do not exceed a single dose of 100 units per kg body weight or a daily dose of 200 units per kg body weight [see Warnings and Precautions (5.1)].

2.2 Preparation and Reconstitution

- Use aseptic technique throughout the entire reconstitution process.
- If the patient uses more than one vial per injection, reconstitute each vial according to the following instructions.
  1. Allow the vials of FEIBA and Sterile Water for Injection (diluent) to reach room temperature, if refrigerated.
  2. Remove the plastic caps from the concentrate and diluent vials.
  3. Wipe the stoppers of both vials with a sterile alcohol swab and allow them to dry prior to use.
  4. Open the package of BAXJECT II Hi-Flow device by peeling away the lid completely without touching the inside (Fig. A). Do not remove the device from the package. Do not touch the clear spike.
  5. Place the diluent vial on a flat and solid surface. Turn the package over and insert the clear plastic spike through the diluent stopper by pressing straight down (Fig. B).
  6. Grip the BAXJECT II Hi-Flow device package at the edges and pull the package off the device (Fig. C). Do not remove the blue protective cap from the BAXJECT II Hi-Flow device. Do not touch the purple spike.
  7. Turn the system over, so that the diluent vial is on top. Quickly insert the purple spike of the BAXJECT II Hi-Flow device fully into the FEIBA vial. The vacuum will draw the diluent into the FEIBA vial (Fig. D). The connection of the two vials should be done expeditiously to close the open fluid pathway created by the first insertion of the spike to the diluent vial.
  8. Gently swirl (do not shake) the vial until FEIBA is completely dissolved. Make sure that FEIBA has been dissolved completely; otherwise, active material will not pass through the device filter. The reconstituted solution should be inspected visually for particulate matter before administration. The solution should be discarded if it is not clear or is discolored.
  9. After reconstitution of FEIBA is complete, the injection or infusion should begin immediately and must be completed within three hours following reconstitution. Do not refrigerate after reconstitution. Discard unused portion.

Figure A

Figure B

Figure C

Figure D

2.3 Administration

For intravenous injection or intravenous infusion after reconstitution only.

- Inspect the reconstituted FEIBA solution visually for particulate matter and discoloration prior to administration. The appearance of the solution should be colorless to slightly yellowish. Do not use if particulate matter or discoloration is observed.
- Flush venous access lines with isotonic saline prior to and after infusion of FEIBA. Do not administer in the same tubing or container with other medicinal products.
- Use plastic Luer lock syringes because protein such as FEIBA tends to stick to the surface of all-glass syringes.
  1. Remove the blue protective cap from the BAXJECT II Hi-Flow device. Tightly connect the syringe to the BAXJECT II Hi-Flow device (DO NOT DRAW AIR INTO THE SYRINGE) by turning the syringe in clockwise direction until stop position. Use of a Luer lock syringe is highly recommended to ensure a tight connection between the syringe and the BAXJECT II Hi-Flow device (Fig. E).
  2. Invert the system so that the dissolved FEIBA product is on top. Draw the dissolved product carefully into the syringe by pulling the plunger back slowly to avoid foaming (Fig. F).
  3. Ensure that the tight connection between the BAXJECT II Hi-Flow device and the syringe is maintained.
  4. Disconnect the syringe.
  5. Attach a suitable needle and inject or infuse intravenously at a rate that does not exceed 10 units per kg of body weight per minute. A syringe pump may be used to control the rate of administration. For a patient with a body weight of 75 kg, this corresponds to an infusion rate up to 15 mL per minute.

Figure E

Figure F

3 DOSAGE FORMS AND STRENGTHS

FEIBA is available as a lyophilized powder in single-dose glass vials containing nominally 500, 1000, or 2500 units per vial.

4 CONTRAINDICATIONS

- Known anaphylactic or severe hypersensitivity reactions to FEIBA or any of its components, including factors of the kinin generating system.
- Disseminated intravascular coagulation (DIC).
- Acute thrombosis or embolism (including myocardial infarction).

5 WARNINGS AND PRECAUTIONS

5.1 Embolic and Thrombotic Events

Thromboembolic events (including venous thrombosis, pulmonary embolism, myocardial infarction, and stroke) can occur with FEIBA, particularly following the administration of high doses (above 200 units per kg per day) and/or in patients with thrombotic risk factors [see Adverse Reactions (6)].

Patients with DIC, advanced atherosclerotic disease, crush injury, septicemia, or concomitant treatment with recombinant factor VIIa have an increased risk of developing thrombotic events due to circulating tissue factor or predisposing coagulopathy. Potential benefit of treatment with FEIBA should be weighed against the potential risk of these thromboembolic events.

Monitor patients receiving more than 100 units per kg of body weight of FEIBA for the development of DIC, acute coronary ischemia and signs and symptoms of other thromboembolic events. If clinical signs or symptoms occur, such as chest pain or pressure, shortness of breath, altered consciousness, vision, or speech, limb or abdomen swelling and/or pain, discontinue the infusion and initiate appropriate diagnostic and therapeutic measures.

The safety and efficacy of FEIBA for breakthrough bleeding in patients receiving emicizumab has not been established. Cases of thrombotic microangiopathy (TMA) were reported in a clinical trial where subjects received FEIBA as part of a treatment regimen for breakthrough bleeding following treatment with emicizumab.^6 Consider the benefits and risks with FEIBA if considered required for patients receiving emicizumab prophylaxis. If treatment with FEIBA is required for patients receiving emicizumab, the hemophilia treating physician should closely monitor for signs and symptoms of TMA. In FEIBA clinical studies thrombotic microangiopathy (TMA) has not been reported.

5.2 Hypersensitivity Reactions

Hypersensitivity and allergic reactions, including severe anaphylactoid reactions, can occur following the infusion of FEIBA. The symptoms include urticaria, angioedema, gastrointestinal manifestations, bronchospasm, and hypotension. These reactions can be severe and systemic (e.g., anaphylaxis with urticaria and angioedema, bronchospasm, and circulatory shock). Other infusion reactions, such as chills, pyrexia, and hypertension have also been reported. If signs and symptoms of severe allergic reactions occur, immediately discontinue administration of FEIBA and provide appropriate supportive care.

5.3 Transmission of Infectious Agents

Because FEIBA is made from human plasma it may carry a risk of transmitting infectious agents, e.g., viruses, and the variant Creutzfeldt-Jakob disease (vCJD) agent, and theoretically, the Creutzfeldt-Jakob disease (CJD) agent. The risk has been minimized by screening plasma donors for prior exposure to certain viruses, by testing for the presence of certain current virus infections and by inactivating and removing certain viruses during the manufacturing process [see Description (11)]. Despite these measures, the product may still potentially transmit human pathogenic agents. There is also the possibility that unknown infectious agents may still be present.

All infections thought by a physician to have been possibly transmitted by this product should be reported by the physician or other healthcare providers to Takeda Pharmaceuticals U.S.A., Inc. at 1-877-TAKEDA-7 (1-877-825-3327) (in the U.S.) and /or to FDA Med Watch (1-800-FDA-1088 or www.fda.gov/medwatch).

5.4 Presence of Isohemagglutinins and Interference with Laboratory Tests

FEIBA contains blood group isohemagglutinins (anti-A and anti-B). Passive transmission of antibodies to erythrocyte antigens, e.g., A, B, D, may interfere with some serological tests for red cell antibodies, such as antiglobulin test (Coombs test).

6 ADVERSE REACTIONS

The most frequently reported adverse reactions observed in >5% of subjects in the prophylaxis trial were anemia, diarrhea, hemarthrosis, hepatitis B surface antibody positive, nausea, and vomiting.

The serious adverse reactions seen with FEIBA are hypersensitivity reactions and thromboembolic events, including stroke, pulmonary embolism and deep vein thrombosis.

6.1 Clinical Trials Experience

Because clinical trials are conducted under widely varying conditions, adverse reaction rates observed in the clinical trials of a drug cannot be directly compared to rates in the clinical trials of another drug and may not reflect the rates observed in clinical practice.

The safety assessment of FEIBA is based on the review of the data from two prospective clinical trials in which FEIBA was used for the treatment of acute bleeding episodes and a prospective trial that compared the use of FEIBA prophylactically versus on-demand treatment.

The adverse reactions reported from two prospective clinical trials in which FEIBA was used for the treatment of acute bleeding episodes were chills, chest pain, chest discomfort, dizziness, dysgeusia, dyspnea, hypoesthesia, increase of inhibitor titer (anamnestic response), nausea, pyrexia, and somnolence. Specifically, the first trial was a multicenter randomized, double-blind trial in 15 hemophilia A subjects with inhibitors to factors VIII. The second trial was a multicenter FEIBA study conducted in 44 hemophilia A subjects with inhibitors, 3 hemophilia B subjects with inhibitors and 2 acquired factor VIII inhibitor subjects. Of the 489 infusions used to treat acute bleeds during the second trial, 18 (3.7%) caused minor transient reactions of chills, fever, nausea, dizziness and dysgeusia. Out of 49 subjects, 10 (20%) had a rise in their inhibitor titers after treatment with FEIBA. Five of these subjects (50%) had increases that were tenfold or more, and 3 (30%) of these subjects received factor VIII or IX concentrates within 2 weeks prior to treatment with FEIBA. These anamnestic rises were not associated with decreased efficacy of FEIBA.

Table 2 lists the adverse reactions in >5% of subjects reported in the randomized, prospective prophylaxis trial comparing FEIBA prophylaxis with on-demand treatment in 36 hemophilia A and B subjects with inhibitors to factors VIII or IX^3. The trial population included 33 (92%) subjects with hemophilia A and 3 (8.3%) subjects with hemophilia B. Four (11%) subjects were ≥7 to <12 years of age, 5 (14%) were ≥12 to <16 years of age, and 27 (75%) were ≥16 years of age. A total of 29 (80.6%) subjects were Caucasian, 3 (8.3%) Asian, 2 (5.6%) Black/African American, and 2 (5.6%) other. The subjects received a total of 4,513 infusions (3,131 for prophylaxis and 1,382 for on-demand).

Table 2: Prophylaxis Study Adverse Reactions (ARs) in >5% of Subjects
MedDRA System Organ Class | Adverse Reaction | Number of ARs | Number of Subjects | Percent of Subjects (N=36)
Blood And Lymphatic System Disorders | Anemia | 2 | 2 | 5.6
Gastrointestinal Disorders | Diarrhea | 2 | 2 | 5.6
Gastrointestinal Disorders | Nausea | 2 | 2 | 5.6
Gastrointestinal Disorders | Vomiting | 2 | 2 | 5.6
Investigations | Hepatitis B Surface Antibody Positive | 4 | 4 | 11.1
Musculoskeletal And Connective Tissue Disorders | Hemarthrosis | 5 | 3 | 8.3

Table 3 lists the adverse reactions and infusion related adverse events reported in >5% of subjects in any of the three groups (50% Reduced Volume, Increased Rate 4 U/kg/min; 50% Reduced Volume, Increased Rate 10 U/kg/min; Overall 50% Reduced Volume) of the randomized, prospective crossover trial evaluating the tolerability and safety of infusing reduced volume of FEIBA at the standard infusion rate of 2 U/kg/min, and at increased rates of 4 and 10 U/kg/min in a total of 33 treated subjects with congenital Hemophilia A with inhibitors.

Table 3: Adverse Reactions (ARs) and Infusion Related Adverse Events in >5% of Subjects, in Patients 18 Years and Older
 | MedDRA System Organ Class | Adverse Reaction | 50% Reduced Volume; Increased Rate 4 U/kg/min (N=30) n (%); m | 50% Reduced Volume; Increased Rate 10 U/kg/min (N=28) n (%); m | Overall 50% Reduced Volume [Includes the following infusion rates: 2 U/kg/min; 4 U/kg/min and 10 U/kg/min] (N=30) n (%); m
Adverse reactions (ARs) | Nervous system disorders | Headache | 0 | 0 | 2 (6.7%); 2
Infusion related AEs | Nervous system disorders | Headache | 0 | 0 | 2 (6.7%); 2
n=Number of subjects, m=number of events

6.2 Postmarketing Experience

The following adverse reactions have been identified during post-approval use of FEIBA. Because postmarketing reporting of adverse reactions is voluntary and from a population of uncertain size, it is not always possible to reliably estimate the frequency of these reactions or establish a causal relationship to product exposure.

Blood and Lymphatic System Disorders: disseminated intravascular coagulation

Cardiac Disorders: tachycardia, flushing

Respiratory, Thoracic, and Mediastinal Disorders: bronchospasm, wheezing

Gastrointestinal Disorders: abdominal discomfort

Skin and Subcutaneous Tissue Disorders: pruritus

General Disorders and Administration Site Conditions: malaise, feeling hot, injection site pain

Investigations: Fibrin D-dimer increased

7 DRUG INTERACTIONS

7.1 Concomitant Medications

Consider the possibility of thrombotic events when systemic antifibrinolytics such as tranexamic acid and aminocaproic acid are used during treatment with FEIBA. No adequate and well-controlled studies of the combined or sequential use of FEIBA and recombinant factor VIIa antifibrinolytics, or emicizumab have been conducted. Use of antifibrinolytics within approximately 6 to 12 hours after the administration of FEIBA is not recommended.

Clinical experience from an emicizumab clinical trial suggests that a potential drug interaction may exist with emicizumab when FEIBA was used as part of a treatment regimen for breakthrough bleeding^6 [see Warnings and Precautions (5.1)].

8 USE IN SPECIFIC POPULATIONS

8.1 Pregnancy

Risk Summary

There are no data with FEIBA use in pregnant women to inform a drug-associated risk. There are no adequate and well-controlled studies in pregnant women. Animal reproduction studies have not been conducted with FEIBA. It is also not known whether FEIBA can cause fetal harm when administered to a pregnant woman or can affect reproductive capacity.

In the U.S. general population, the estimated background risk for major birth defects and miscarriage in clinically recognized pregnancies is 2-4% and 15-20%, respectively.

There is no information available on the effect of FEIBA on labor and delivery.

8.2 Lactation

Risk Summary

There is no information regarding the presence of FEIBA in human milk, the effect on the breastfed child, or the effects on milk production.

The developmental and health benefits of breastfeeding should be considered along with the mother's clinical need for FEIBA and any potential adverse effects on the breastfed child from FEIBA or from the underlying condition.

8.4 Pediatric Use

Safety and efficacy of FEIBA have been evaluated in nine pediatric subjects treated in the routine prophylaxis trial including 4 subjects ≥7 to <12 years of age and 5 subjects ≥12 to <16 years of age. The dosing for all pediatric subjects was based on body weight. A total of 576 infusions were given for the treatment of 223 bleeding episodes (504 infusions for joint bleeding episodes, 72 infusions for muscle and soft tissue bleeding episodes). In 223 (100%) of the episodes, hemostasis was achieved with one or more infusions. Hemostatic efficacy was rated as excellent or good in a majority (96.9%) of the bleeding episodes in both regimens at 24 hours post infusion. The median annualized bleeding episode rate (ABR) for children ≥7 to <12 years of age was 7.7 bleeds per patient per year, as compared to 39 for subjects treated with on-demand therapy [see Clinical Studies (14)].

The safety and efficacy of FEIBA has not been evaluated in neonates.

8.5 Geriatric Use

The safety and efficacy of FEIBA has not been evaluated in subjects ≥65 years of age.

11 DESCRIPTION

FEIBA (Anti-Inhibitor Coagulant Complex) is a freeze-dried sterile human plasma fraction with factor VIII inhibitor bypassing activity to be reconstituted for intravenous administration. Factor VIII inhibitor bypassing activity is expressed in arbitrary units. One unit of activity is defined as that amount of FEIBA that shortens the aPTT of high titer factor VIII inhibitor reference plasma to 50% of the blank value.

FEIBA contains mainly non-activated factors II, IX, and X and mainly activated factor VII. It contains approximately equal unitages of factor VIII inhibitor bypassing activity and prothrombin complex factors. In addition, the preparation contains 1-6 units of factor VIII coagulant antigen (FVIII C:Ag) per mL. The product contains traces of factors of the kinin generating system. It contains no heparin. Reconstituted FEIBA contains 4 mg of trisodium citrate and 8 mg of sodium chloride per mL.

FEIBA is manufactured from large pools of human plasma. Screening against potentially infectious agents begins with the donor selection process and continues throughout plasma collection and plasma preparation. Each individual plasma donation used in the manufacture of FEIBA is collected at FDA approved blood establishments and is tested by FDA licensed serological tests for Hepatitis B Surface Antigen (HBsAg), and for antibodies to Human Immunodeficiency Virus (HIV-1/HIV-2) and Hepatitis C Virus (HCV) Mini-pools of the plasma are tested and found negative for the presence of HIV-1 and HCV by FDA licensed Nucleic Acid Testing (NAT).

To reduce the risk of viral transmission, the manufacturing process of FEIBA includes two dedicated and independent virus removal/inactivation steps namely 35 nm nanofiltration and a vapor heat treatment process. In addition, the DEAE-Sephadex adsorption contributes to the virus safety profile of FEIBA.

In vitro spiking studies have been used to validate the capability of the manufacturing process to remove and inactivate viruses. Table 4 summarizes the results of the viral clearance studies for FEIBA.

Table 4: Virus Reduction Factors (log10) During Manufacturing FEIBA
Virus Type | Enveloped RNA |  |  | Enveloped DNA | Non-enveloped RNA | Non-enveloped DNA
Virus Family | Retroviridae | Flaviviridae |  | Herpesviridae | Picornaviridae | Parvoviridae
Virus [Abbreviations: HIV-1, Human Immunodeficiency Virus Type 1; BVDV, Bovine Viral Diarrhea Virus (model for Hepatitis C Virus and other lipid enveloped RNA viruses); WNV, West Nile Virus; PRV, Pseudo rabies Virus (model for lipid enveloped DNA viruses, including Hepatitis B Virus); HAV, Hepatitis A Virus; MMV, Mice Minute Virus (model for non-lipid enveloped DNA viruses, including B19 virus [B19V]). ND not done] | HIV-1 | BVDV | WNV | PRV | HAV | B19V [Reduction factor for Parvovirus B19 claimed for the Vapor Heat Treatment is based on results derived from experimental infectivity and titration assays.] | MMV
DEAE Sephadex Adsorption | 3.2 | 1.8 | ND | 2.5 | 1.5 | 1.7 | 1.2
35 nm Nanofiltration | >5.3 | 2.1 | 4.7 | >5.7 | 2.6 | 0.2 [Reduction factors <1 log are not used for calculation of the overall reduction factor.] | 1.0
Vapor-Heat Treatment | >5.9 | >5.6 | >8.1 | >6.7 | >5.2 | 3.5 | 0.9
Overall virus reduction factor (log10) | >14.4 | >9.5 | >12.8 | >14.9 | >9.3 | 5.2 | 2.2

12 CLINICAL PHARMACOLOGY

12.1 Mechanism of Action

The mechanism of action of FEIBA is still the subject of scientific discussion. FEIBA contains multiple components, mainly non-activated factors II, IX, X and mainly activated factor VII. These factors can interact with plasma coagulation factors and platelets to increase the impaired thrombin generation of hemophilia patients with inhibitors, leading to hemostasis.

12.2 Pharmacodynamics

Laboratory assessment of coagulation does not necessarily correlate with or predict the hemostatic effectiveness of FEIBA. Factor VIII inhibitor bypassing activity of FEIBA has been demonstrated in vitro as well as in vivo. FEIBA can shorten the activated partial thromboplastin time (aPTT) and increase the thrombin generation in plasma containing factor VIII inhibitor.^4,5

12.3 Pharmacokinetics

FEIBA is composed of different coagulation factors, with varying half-lives for the individual components. The pharmacokinetic properties of FEIBA have not been formally studied in humans.

13 NONCLINICAL TOXICOLOGY

13.1 Carcinogenesis, Mutagenesis, Impairment of Fertility

Long-term animal studies to evaluate the carcinogenic potential of FEIBA or studies to determine the genotoxicity or the effect of FEIBA on fertility have not been performed. An assessment of the carcinogenic potential of FEIBA was completed to demonstrate minimal carcinogenic risk from product use.

14 CLINICAL STUDIES

Control and Prevention of Bleeding Episodes

The efficacy of FEIBA in the treatment of bleeding episodes has been demonstrated by two prospective clinical trials.^1,2

The first trial was a multicenter, randomized, double-blind trial comparing the effect of FEIBA and a non-activated prothrombin complex concentrate in 15 subjects with hemophilia A and inhibitors to factor VIII. The inclusion criteria were history of high titer inhibitors, high responder status, more than 1 bleeding episode per month in the prior year and no signs of liver failure. A total of 150 bleeding episodes including 117 joint, 20 musculoskeletal and 4 mucocutaneous bleeds, were treated. A single dose of 88 units per kg of body weight was used uniformly for treatments with FEIBA. A second treatment was allowed for muscle bleeds after 12 hours and 6 hours after mucocutaneous bleeds, if necessary.

Subjects and investigators were asked to rate hemostatic efficacy based on a scale of effective, partially effective, not effective or not sure. The criteria for evaluation of the effectiveness were severity of pain, subjective improvement, circumference of muscle or joint, restriction of joint mobility, cessation of open bleeding, start of rebleeding and quantity and nature of analgesics. FEIBA was effective in 41% and partly effective in 25% of episodes (i.e. combined effectiveness of 66%), while prothrombin complex concentrate was rated effective in 25% and partly effective in 21% of episodes (i.e., combined effectiveness of 46%).

The second trial with FEIBA was a multicenter randomized, prospective trial. This trial was conducted in 44 hemophilia A subjects with inhibitors, 3 hemophilia B subjects with inhibitors and 2 acquired factor VIII inhibitor subjects. It was designed to evaluate the efficacy of FEIBA in the treatment of joint, mucous membrane, musculocutaneous and emergency bleeding episodes such as central nervous system hemorrhages and surgical bleedings. The inclusion criteria used were age >4 years, history of inhibitor titer ≥4 Bethesda Units (BU) and without chronic liver disease. Subjects were excluded if they had a history of thromboembolic events or allergic reactions to FEIBA.

Forty-nine (49) subjects with inhibitor titers of greater than 5 BU were enrolled from nine co-operating hemophilia centers. Subjects were treated with 50 units per kg of body weight, repeated at 12-hour intervals (6-hour intervals in mucous membrane bleedings), if necessary. A total of 489 infusions were given for the treatment of 165 bleeding episodes (102 joint, 33 muscle and soft tissue, 20 mucous membrane, and 10 emergency bleeds, including 3 central nervous system bleeds and 4 surgical procedures). Bleeding was controlled in 153 episodes (93%). In 130 (78%) of the episodes, hemostasis was achieved with one or more infusions within 36 hours. Of these, 36% were controlled with one infusion within 12 hours. An additional 14% of episodes responded after more than 36 hours.

Routine Prophylaxis

In a multicenter, open-label, prospective, randomized clinical trial comparing subjects receiving FEIBA for prophylaxis with subjects receiving FEIBA for on-demand treatment, 36 hemophilia A and B subjects with inhibitors to factor VIII or IX were analyzed in the intent-to-treat analysis. Study population included 29 (80.6%) Caucasian, 3 (8.3%) Asian, 2 (5.6%) Black/African American, and 2 (5.6%) other. Inclusion criteria were subjects with a history of high titer inhibitors or low titer refractory to increased factor VIII or IX dosing, age range between 4 and 65, and subjects receiving bypassing agents with ≥12 bleeds in the 12 months prior to trial entry. Subjects with a history of thromboembolic events, symptomatic liver disease, or a platelet count <100,000 per mL, and those receiving immune tolerance induction or routine prophylaxis were excluded.

Subjects were randomized to receive 12 months of prophylactic or on-demand treatment with FEIBA. Seventeen subjects randomized to the prophylaxis arm received 85 units per kg of FEIBA every other day. Nineteen subjects randomized to the on-demand arm received FEIBA for the treatment of acute bleeding episodes per the dose and dosing regimen recommended. Target joints were defined as ≥4 bleeding episodes within 6 months. In this trial, ankles, knees, elbows and hips were target joint locations. Preexisting target joints were not considered as new target joints.

Hemostatic efficacy for treatment of acute bleeds was evaluated at 6 and 24 hours according to a pre-specified four-point scale of excellent, good, fair, or none. An evaluation of "none" was considered a treatment failure. The criteria for evaluation of the effectiveness were relief of pain, cessation of bleeding, and number of infusions required to treat a bleed.

A total of 825 bleeding episodes were reported including 196 that occurred during prophylaxis and 629 that occurred during on-demand therapy. A majority (78%) of the 794 bleeding episodes that were rated for efficacy were treated with 1 or 2 infusions. Hemostatic efficacy was rated as excellent or good for 74% of bleeding episodes rated at 6 hours post infusion and for 87% of the bleeding episodes at 24 hour post infusion. A total of 19 (2.4%) bleeds were rated as "none" at 6 hours post infusion; 1 bleed (0.1%) was rated "none" at 24 hours.

Hemostatic efficacy for routine prophylaxis was evaluated against subjects who received on-demand therapy.

The overall median annual bleed rate (ABR) for the on-demand arm was 28.7 compared to 7.9 for the prophylaxis arm, which represents a 72% reduction in median ABR with prophylaxis. When analyzed by site (e.g. joint, non-joint) and cause of bleed (e.g. spontaneous, traumatic), prophylactic treatment with FEIBA resulted in a greater than 50% reduction in ABR. There were fewer subjects in the prophylaxis arm who developed new target joints (7 new target joints in 5 subjects treated with prophylaxis compared to 23 new target joints in 11 subjects in the on-demand arm). Target joints developed in two subjects in the on-demand arm and three in the prophylaxis arm who did not have reported target joints at trial enrollment. A total of 3 of 17 (18%) subjects had no bleeding episodes on prophylaxis. In the on-demand arm, all subjects experienced a bleeding episode.

ABR by age category between on-demand and prophylaxis regimens is provided in Table 5. One adolescent subject on prophylaxis had a higher rate of bleeding possibly due to increased physical activity after study enrollment.

Table 5: ABR by Age Category
Age Category | On-Demand: Number of Subjects | On-Demand: ABR Median | Prophylaxis: Number of Subjects | Prophylaxis: ABR Median
Children (≥7 to <12 years old) | 2 | 39.3 | 2 | 7.7
Adolescent (≥12 to <16 years old) | 2 | 30.9 | 3 | 27.5
Adult (≥16 years old) | 15 | 23.9 | 12 | 6.9

15 REFERENCES

1. Sjamsoedin LJ, Heijnen L, Mauser-Bunschoten EP, van Geijlswijk JL, van Houwelingen H, van Asten P, Sixma JJ. The effect of Activated Prothrombin-Complex Concentrate (FEIBA) on joint and muscle bleeding in patients with Hemophilia A and antibodies to Factor VIII. N Engl J Med. 1981;305(13): 717-721.
2. Hilgartner MW, Knatterud GL. The use of Factor-Eight-Inhibitor-By-Passing-Activity (FEIBA IMMUNO) product for treatment of bleeding episodes in Hemophiliacs with inhibitors. Blood. 1983;61(1): 36-40.
3. Antunes SV, Tangada S, Stasyshyn O, Mamonov V, Phillips J, Guzman-Becerra N, Grigorian A, Ewenstein B, Wong WY. Randomized comparison of prophylaxis and on-demand regimens with FEIBA NF in the treatment of haemophilia A and B with inhibitors. Haemophilia. 2013; DOI 10.1111/hae.12246.
4. Turecek PL, Varadi K, Gritsch H, Auer W, Pichler L, Eder G, Schwarz HP. Factor Xa and prothrombin: mechanism of action of FEIBA. Vox Sanguinis 1999;77 Suppl 1:72-79.
5. Turecek PL, Varadi K, Gritch H, Schwarz HP. FEIBA: Mode of action Haemophilia 2004;10: Suppl. 2:3-9
6. Oldenburg et al. Emicizumab Prophylaxis in Hemophilia A with Inhibitors. N Engl J Med 2017:377:809-818.

16 HOW SUPPLIED/STORAGE AND HANDLING

How Supplied

FEIBA is available in single-dose vials in the following nominal dosage strengths:

Nominal Strength | Color Code | Factor VIII Potency Range | Kit NDC | Sterile Water Volume
500 units | Orange | 350-650 units per vial | 64193-426-02 | 10 mL
1000 units | Green | 700-1300 units per vial | 64193-424-02 | 20 mL
2500 units | Purple | 1750-3250 units per vial | 64193-425-02 | 50 mL

The number of units of factor VIII inhibitor bypassing activity is stated on the label of each vial.

FEIBA is packaged with a suitable volume (10 mL, 20 mL, or 50 mL) of Sterile Water for Injection, U.S.P., one BAXJECT II Hi-Flow Needleless Transfer Device, and one Package Insert.

Not made with natural rubber latex.

Storage and Handling

- Store at 36°F to 77°F (2°C to 25°C)
- Store in the original package in order to protect from light.
- Do not freeze.
- Prior to preparation and reconstitution, allow the vials of FEIBA and Sterile Water for Injection (diluent) to reach room temperature, if refrigerated.

17 PATIENT COUNSELING INFORMATION

Inform patients:

- of the signs and symptoms of thrombosis, such as chest pain or pressure, shortness of breath, altered consciousness, vision, or speech, limb or abdomen swelling and/or pain. Advise patients to seek immediate medical attention if any of these symptoms occur.
- of the signs and symptoms of hypersensitivity reactions, such as urticaria, angioedema, gastrointestinal manifestations, bronchospasm, and hypotension. Advise patients to discontinue use of the product if these symptoms occur and seek immediate emergency treatment.
- that because FEIBA is made from human blood, it may carry a risk of transmitting infectious agents, e.g., viruses, the variant Creutzfeldt-Jakob disease (vCJD) agent, and theoretically, the Creutzfeldt-Jakob disease (CJD) agent.
- if they are on emicizumab prophylaxis therapy and need FEIBA to treat a breakthrough bleeding episode then they must be monitored by their hemophilia treating physician, preferably at the hemophilia treatment center (HTC).
- to report any adverse reactions or problems following FEIBA administration to their hemophilia treating physician.

To enroll in the confidential, Industry-wide Patient Notification System, call 1-888-873-2838.

Takeda Pharmaceuticals U.S.A., Inc.
Cambridge, MA 02142
U.S. License No. 1898

FEIBA is a registered trademark of Baxalta Incorporated.

Takeda and are registered trademarks of Takeda Pharmaceutical Company Limited.

©2024 Takeda Pharmaceutical Company Limited. All rights reserved.

PRINCIPAL DISPLAY PANEL - Kit Carton

20 mL size, dried
NDC 64193-424-02

Anti-Inhibitor Coagulant Complex
FEIBA

Nanofiltered & Vapor Heated

For Intravenous Use After Reconstitution
Contains no preservative

Dosage and Administration: See accompanying package insert.

Storage: 36°F to 77°F (2°C to 25°C). Store in the original package in order to protect from light.

Reconstitution: Use 20 mL sWFI, U.S.P.;Do not refrigerate after reconstitution.; Use within 3 hours of
reconstitution.

Do Not Freeze

Rx Only

Takeda

Includes
BAXJECT II Hi-Flow
Needleless Transfer Device

PRINCIPAL DISPLAY PANEL - 20 mL Vial Label

20 mL size, dried
NDC 64193-324-01

Anti-Inhibitor Coagulant Complex
FEIBA
Nanofiltered & Vapor Heated

For Intravenous Use After Reconstitution
Contains no preservative

Dosage & Administration: See accompanying package insert.

Storage: 36°F to 77°F (2°C to 25°C).

Reconstitution: Use 20 mL sWFI, U.S.P.; Do not refrigerate
after reconstitution.; Use within 3 hours of reconstitution.

Rx only
0754401

PRINCIPAL DISPLAY PANEL - Kit Carton

Single-dose vial
NDC 64193-425-02

Anti-Inhibitor Coagulant Complex
FEIBA

Nanofiltered & Vapor Heated

For Intravenous Use After Reconstitution
Contains no preservative

Dosage and Administration: See accompanying package insert.

Storage: 36°F to 77°F (2°C to 25°C).
Store in the original package in order to protect from light.

Reconstitution: Use 50 mL sWFI, U.S.P.; Do not refrigerate after reconstitution.; Use within 3 hours of
reconstitution.

Do Not Freeze

Rx Only

Takeda

Includes
BAXJECT II Hi-Flow
Needleless Transfer Device

PRINCIPAL DISPLAY PANEL - 50 mL Vial Label

50 mL size, dried
NDC 64193-325-01

Anti-Inhibitor Coagulant Complex
FEIBA
Nanofiltered & Vapor Heated

For Intravenous Use After Reconstitution
Contains no preservative

Dosage & Administration: See accompanying package insert.

Storage: 36°F to 77°F (2°C to 25°C).

Reconstitution: Use 50 mL sWFI, U.S.P.; Do not refrigerate
after reconstitution.; Use within 3 hours of reconstitution.

Rx only
0754404

PRINCIPAL DISPLAY PANEL - Kit Carton

Single-dose vial
NDC 64193-426-02

Anti-Inhibitor
Coagulant Complex
FEIBA

Nanofiltered & Vapor Heated

For Intravenous Use After Reconstitution
Contains no preservative

Dosage and Administration: See accompanying package insert.

Storage: 36°F to 77°F (2°C to 25°C). Store in the original package in order to protect
from light.

Reconstitution: Use 10 mL sWFI, U.S.P.; Do not refrigerate after reconstitution.; Use within
3 hours of reconstitution.

Do Not Freeze

Rx Only

Takeda

Includes
BAXJECT II Hi-Flow
Needleless Transfer Device

PRINCIPAL DISPLAY PANEL - 10 mL Vial Label

Single-dose vial
NDC 64193-326-01

Anti-Inhibitor Coagulant Complex
FEIBA
Nanofiltered & Vapor Heated

For Intravenous Use After Reconstitution
No preservative

Dosage & Administration: See accompanying package insert.

Storage: 36°F to 77°F (2°C to 25°C).

Reconstitution: Use 10 mL sWFI, U.S.P.; Do not refrigerate after
reconstitution.; Use within 3 hours of reconstitution.

Rx only
Takeda
0754406